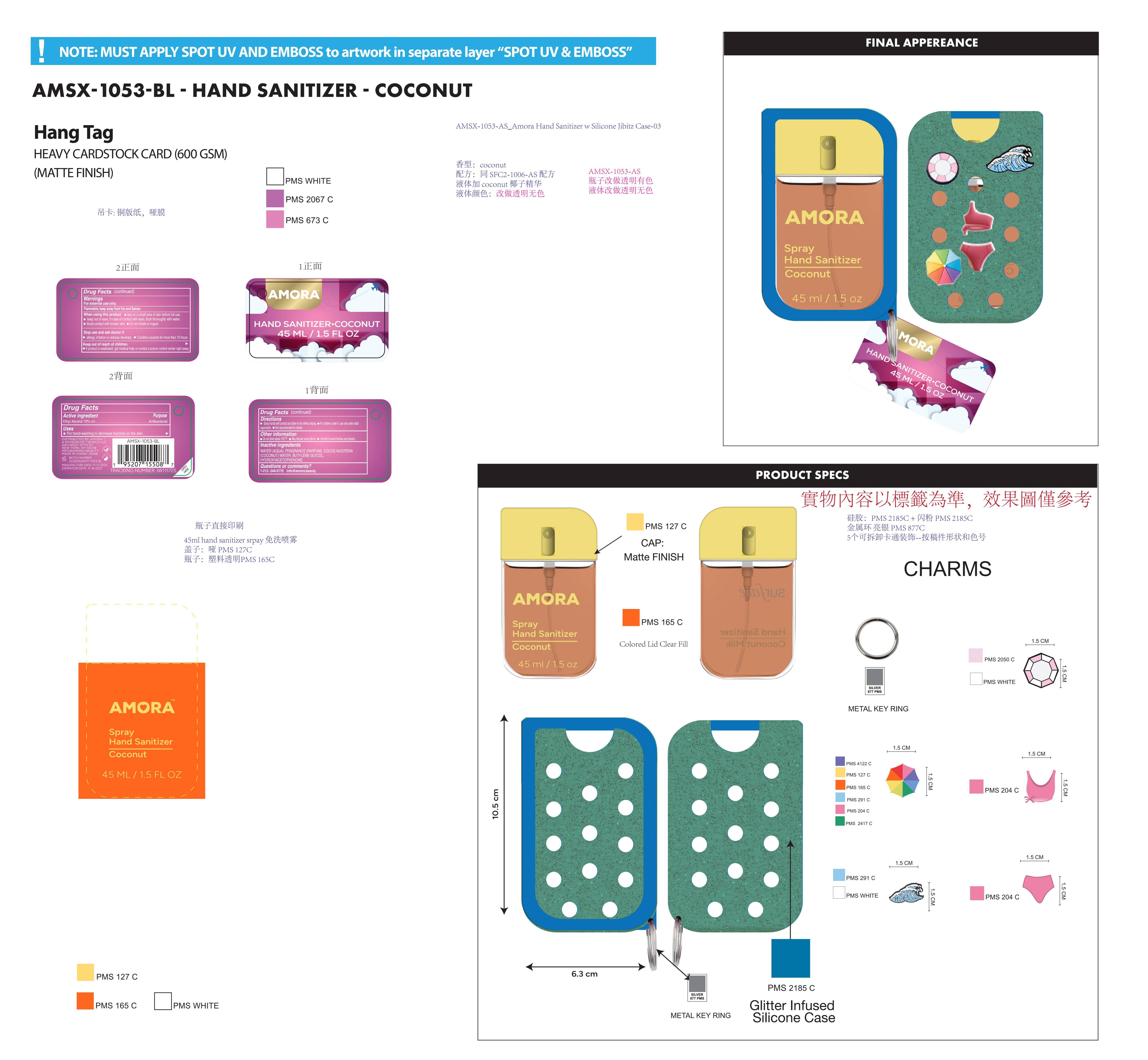 DRUG LABEL: AMORA Spray. Hand Sanitizer coconut
NDC: 85161-141 | Form: SPRAY
Manufacturer: Longway Technology(Guangzhou) Co., Ltd.
Category: otc | Type: HUMAN OTC DRUG LABEL
Date: 20251202

ACTIVE INGREDIENTS: ALCOHOL 0.7 mL/1 mL
INACTIVE INGREDIENTS: HYDROXYACETOPHENONE; BUTYLENE GLYCOL; COCONUT WATER; WATER; FRAGRANCE 13576

ACTIVE INGREDIENT

Ethyl Alcohol 70% v/v

PURPOSE

Antibacterial

KEEP OUT OF REACH OF CHILDREN

If product is swallowed, get medical help or contact a poison control center right away.

INACTIVE INGREDIENT

WATER (AQUA), FRAGRANCE (PARFUM), COCOS NUCIFERA (COCONUT) WATER, BUTYLENE GLYCOL, HYDROXYACETOPHENONE.

WARNINGS

For external use only.
Flammable, keep away from fire and flames

When using this product

test on a small area of skin before full use.

keep out of eyes. In case of contact with eyes, flush thoroughly with water.
Avoid contact with broken skin.

Do not inhale or ingest.

Stop use and ask doctor if

allergy, irritation or redness develops.

Condition persists for more than 72 hours.

Keep out of reach of children.
lf product is swallowed, get medical help or contact a poison control center right away.

OTHER SAFETY INFORMATION

Do not store above 105°F
May discolor some fabrics

Harmful to wood finishes and plastics

Directions

Spray hands with product and allow to dry without wiping.

For children under 6, use only under adult supervision.

- Not recommended for infants.

QUESTIONS

1-212-244-5170 info@amora.beauty

INDICATIONS AND USAGE

For hand-washing to decrease bacteria on the skin.